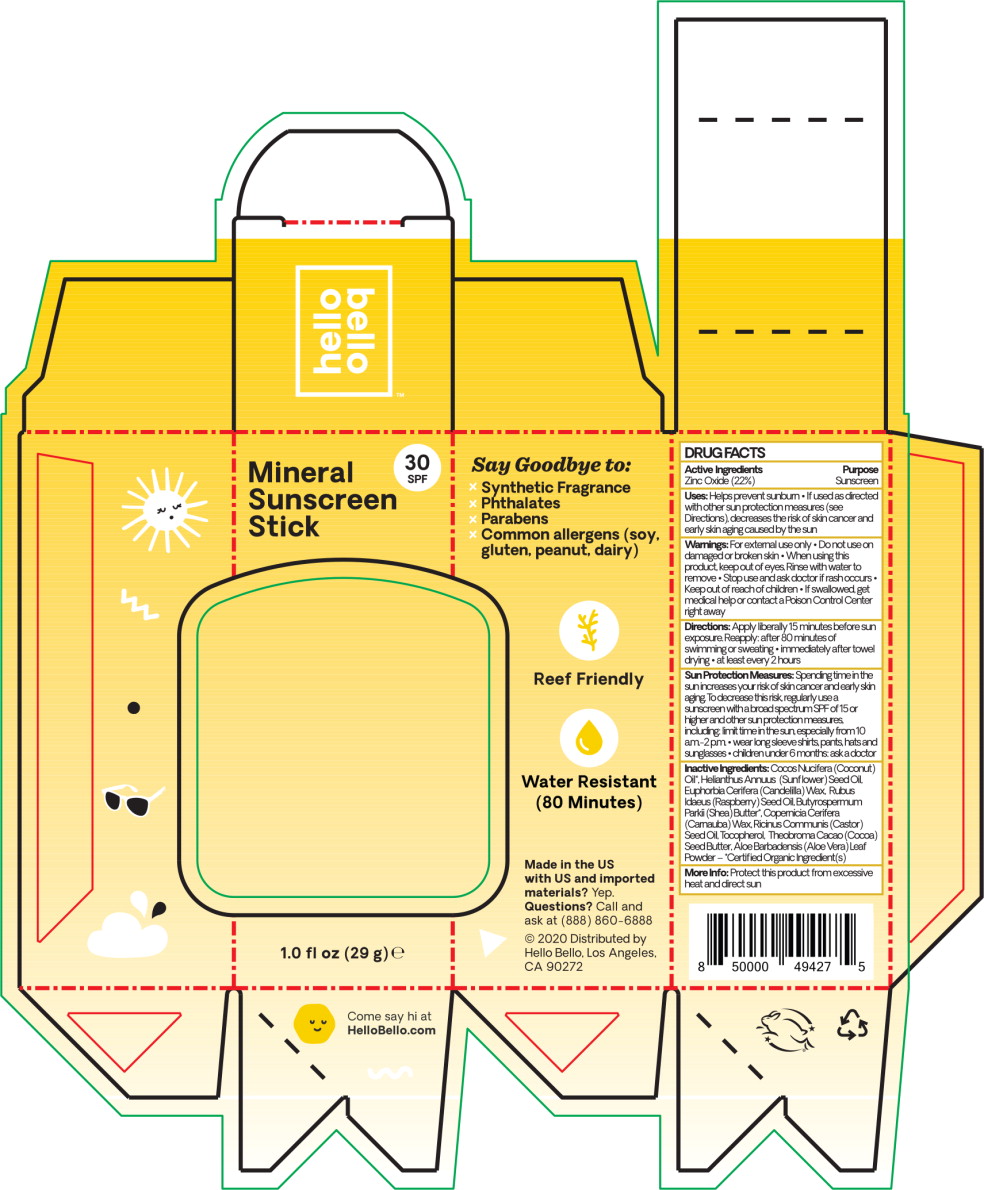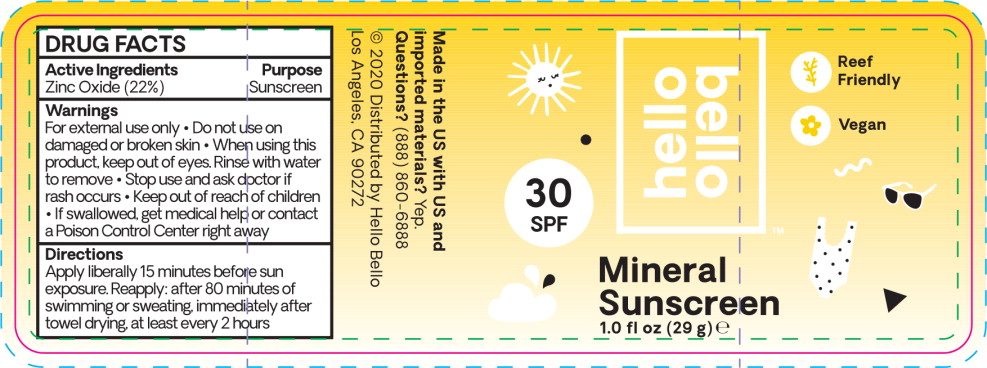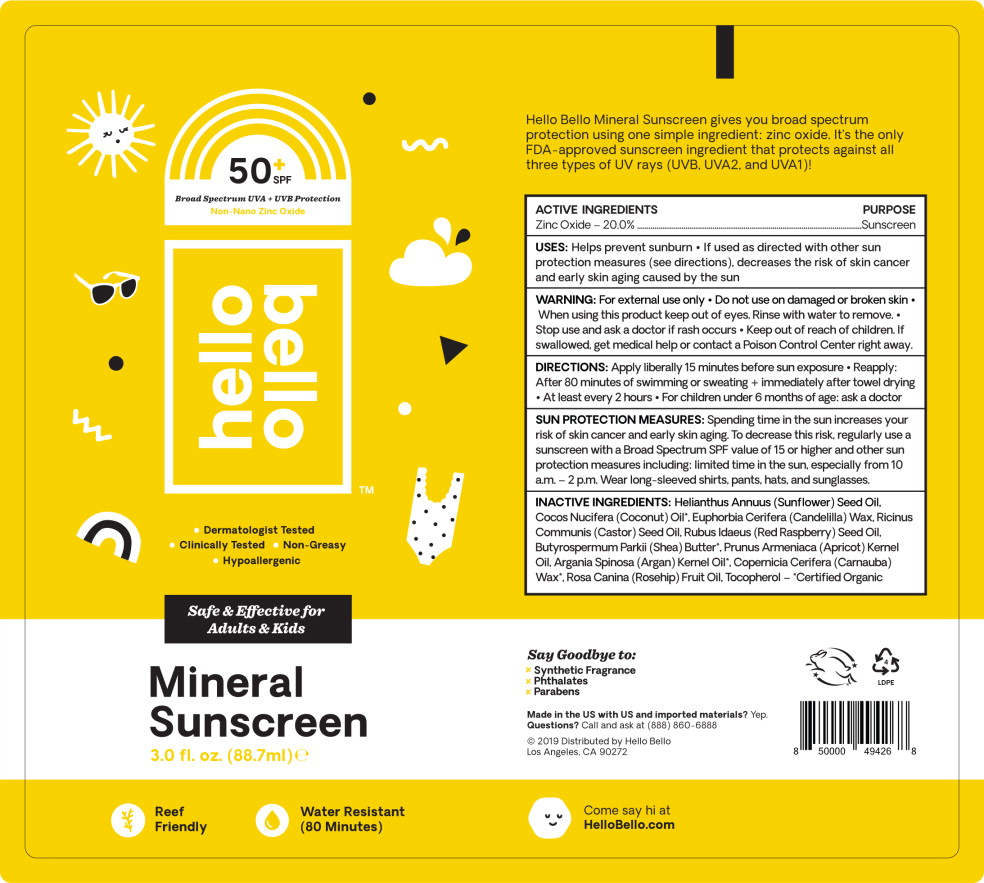 DRUG LABEL: Zinc Oxide
NDC: 73418-020 | Form: STICK
Manufacturer: Hello Bello
Category: otc | Type: HUMAN OTC DRUG LABEL
Date: 20210113

ACTIVE INGREDIENTS: Zinc Oxide 22 g/100 mL
INACTIVE INGREDIENTS: Sunflower Oil; Coconut Oil; Candelilla Wax; Castor Oil; Raspberry Seed Oil; Apricot Kernel Oil; Argan Oil; Carnauba Wax; Aloe Vera Leaf; Tocopherol

Drug Facts

ACTIVE INGREDIENTS

Zinc Oxide - 20.0%

PURPOSE

Sunscreen

USES:

Helps prevent sunburn

- If used as directed with other sun protection measures (see directions), decreases the risk of skin cancer and early skin aging caused by the sun

WARNING:

For external use only

- Do not use on damaged or broken skin

- When using this product keep out of eyes. Rinse with water to remove.

- Stop use and ask a doctor if rash occurs

- Keep out of reach of children. If swallowed, get medical help or contact a Poison Control Center right away.

DIRECTIONS:

Apply liberally 15 minutes before sun exposure

- Reapply: After 80 minutes of swimming or sweating + immediately after towel drying
- At least every 2 hours
- For children under 6 months of age: ask a doctor

SUN PROTECTION MEASURES:

Spending time in the sun increases your risk of skin cancer and early skin aging. To decrease this risk, regularly use a sunscreen with a Broad Spectrum SPF value of 15 or higher and other sun protection measures including: limited time in the sun, especially from 10 am. - 2 p.m. Wear long-sleeved shirts, pants, hats, and sunglasses.

INACTIVE INGREDIENTS:

Helianthus Annuus (Sunflower) Seed Oil, Cocos Nucifera (Coconut) Oil*, Euphorbia Cerifera (Candelilla) Wax, Ricinus Communis (Castor) Seed Oil, Rubus Idaeus (Red Raspberry) Seed Oil, Butyrospermum Parkii (Shea) Butter*, Prunus Armeniaca (Apricot) Kernel Oil, Argania Spinosa (Argan) Kernel Oil*, Copernicia Cerifera (Carnauba) Wax*, Rosa Canina (Rosehip) Fruit Oil, Tocopherol - *Certified Organic

Principal Display Panel - 29 g Box Label

hello
bello

Mineral
Sunscreen
Stick

30
SPF

1.0 fl oz (29 g) e

Principal Display Panel - 29 g Stick Label

hello
bello

Mineral
Sunscreen
Stick

30
SPF

1.0 fl oz (29 g) e

Reef
Friendly

Vegan

Principal Display Panel - 88.7 mL Carton Label

50+
SPF

Broad Spectrum UVA + UVB Protection

Non- Nano Zinc Oxide

hello
bello™

• Dermatologist Tested

• Clinically Tested • Non-Greasy

• Hypoallergenic

Safe & Effective for
Adults & Kids

Mineral
Sunscreen

3.0 fl. oz. (88.7 ml) e

Reef
Friendly

Water Resistant
(80 Minutes)